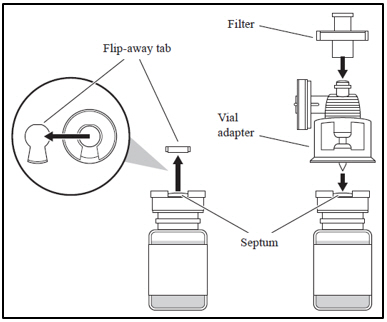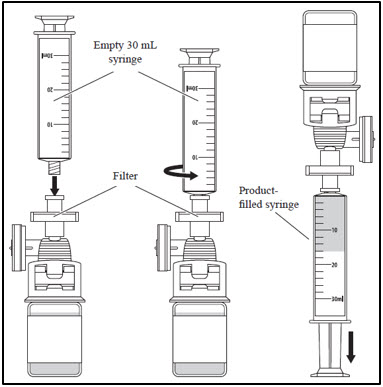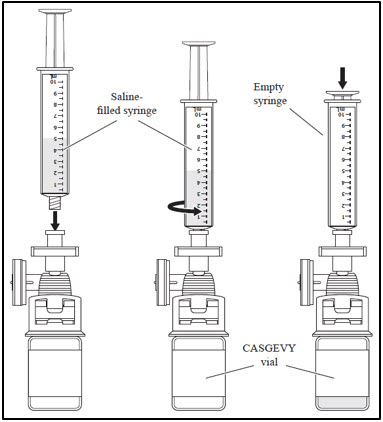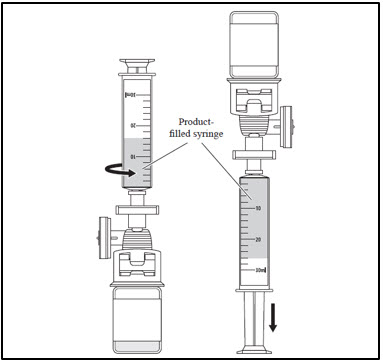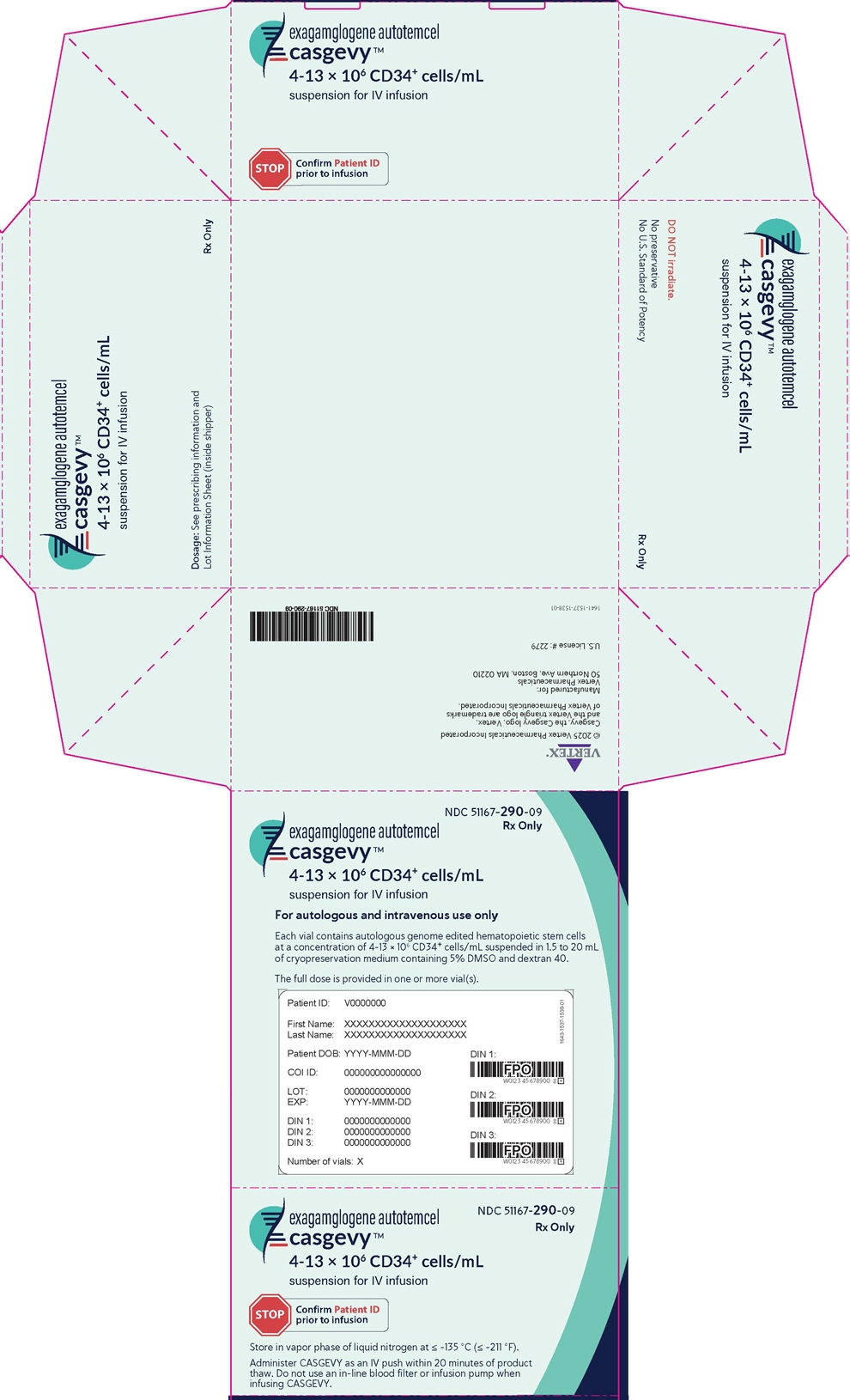 DRUG LABEL: CASGEVY
NDC: 51167-290 | Form: INJECTION, SUSPENSION
Manufacturer: Vertex Pharmaceuticals Incorporated
Category: other | Type: CELLULAR THERAPY
Date: 20251212

ACTIVE INGREDIENTS: exagamglogene autotemcel 13000000 1/1 mL

HIGHLIGHTS OF PRESCRIBING INFORMATION

These highlights do not include all the information needed to use CASGEVY™ safely and effectively. See full prescribing information for CASGEVY
CASGEVY (exagamglogene autotemcel), suspension for intravenous infusion
Initial U.S. Approval: 2023

RECENT MAJOR CHANGES

Warnings and Precautions, Off-Target Genome Editing Risk (5.4) | 08/2025

1. INDICATIONS AND USAGE

CASGEVY is an autologous genome edited hematopoietic stem cell-based gene therapy indicated for the treatment of patients aged 12 years and older with:

- sickle cell disease (SCD) with recurrent vaso-occlusive crises (VOCs). (1)
- transfusion-dependent β-thalassemia (TDT). (1)

2 DOSAGE AND ADMINISTRATION

For autologous use only. For intravenous use only.

- Patients are required to undergo hematopoietic stem cell (HSC) mobilization followed by apheresis to obtain CD34^+ cells for CASGEVY manufacturing. (2.2)
- Dosing of CASGEVY is based on body weight. The minimum recommended dose is 3 × 10^6 CD34^+ cells/kg. (2.1, 2.3)
- Full myeloablative conditioning must be administered between 48 hours and 7 days before infusion of CASGEVY. (2.2)
- Prophylaxis for seizures should be considered prior to initiating myeloablative conditioning. (2.2)
- Verify that the patient's identity matches the unique patient identification information on the product labels and Lot Information Sheet prior to thaw and infusion. (2.2)
- Do not sample, alter, or irradiate CASGEVY. (2.2)
- Do not use an in-line blood filter when infusing CASGEVY. (2.3)
- Administer each vial of CASGEVY via intravenous infusion within 20 minutes of thaw. (2.3)

3 DOSAGE FORMS AND STRENGTHS

- CASGEVY is a cell suspension for intravenous infusion. (3)
- The minimum recommended dose of CASGEVY is 3 × 10^6 CD34^+ cells per kg of body weight, which may be composed of multiple vials. (3)

4 CONTRAINDICATIONS

- None. (4)

5 WARNINGS AND PRECAUTIONS

- Neutrophil Engraftment Failure: Monitor absolute neutrophil counts (ANC) after CASGEVY infusion. Administer rescue cells in the event of neutrophil engraftment failure. (5.1)
- Delayed Platelet Engraftment: Monitor platelet counts until platelet engraftment and recovery are achieved. Patients should be monitored for bleeding. (5.2)
- Hypersensitivity Reactions: Monitor for hypersensitivity reactions during and after infusion. (5.3)
- Off-Target Genome Editing Risk: The risk of unintended, off-target editing in CD34^+cells due to genetic variants cannot be ruled out. (5.4)

6 ADVERSE REACTIONS

The most common Grade 3 or 4 non-laboratory adverse reactions (incidence ≥ 25%) were mucositis and febrile neutropenia in patients with SCD and TDT, and decreased appetite in patients with SCD. (6)

The most common Grade 3 or 4 laboratory abnormalities (≥ 50%) were neutropenia, thrombocytopenia, leukopenia, anemia, and lymphopenia. (6)

To report SUSPECTED ADVERSE REACTIONS, contact Vertex Pharmaceuticals Incorporated at 1-877-634-8789 or FDA at 1-800-FDA-1088 or www.fda.gov/medwatch.

7 DRUG INTERACTIONS

- Granulocyte-Colony Stimulating Factor: Granulocyte-Colony Stimulating Factor (G-CSF) must not be used for CD34^+ HSC mobilization of patients with SCD. (7.1)
- Hydroxyurea: Discontinue hydroxyurea at least 8 weeks prior to start of mobilization and conditioning. (7.2)
- Voxelotor and Crizanlizumab: Discontinue the use of voxelotor and crizanlizumab at least 8 weeks prior to start of mobilization and conditioning. (7.3)
- Iron Chelators: Discontinue iron chelators at least 7 days prior to initiation of myeloablative conditioning. Avoid the use of non-myelosuppressive iron chelators for at least 3 months and use of myelosuppressive iron chelators for at least 6 months after CASGEVY infusion. (7.4)

FULL PRESCRIBING INFORMATION

1. INDICATIONS AND USAGE

CASGEVY is indicated for the treatment of patients aged 12 years and older with:

- sickle cell disease (SCD) with recurrent vaso-occlusive crises
- transfusion-dependent β-thalassemia (TDT)

2 DOSAGE AND ADMINISTRATION

2.1 Dose

For autologous use only. For one-time, single dose intravenous use only.

The minimum recommended dose of CASGEVY is 3 × 10^6 CD34^+ cells/kg.

CASGEVY is provided as a single dose for infusion containing a suspension of CD34^+ cells in one or more vials. See the Lot Information Sheet provided with the product shipment for additional information pertaining to the number of vials required to achieve the patient-specific dose. Administer all vials.

2.2 Preparation Before CASGEVY Infusion

Confirm that hematopoietic stem cell (HSC) transplantation is appropriate for the patient before mobilization, apheresis and myeloablative conditioning are initiated.

Screen patients for HIV-1, HIV-2, HBV, HCV, and any other infectious agents in accordance with local guidelines before collection of cells for manufacturing. CASGEVY should not be used in patients with active HIV-1, HIV-2, HBV or HCV.

Discontinue disease modifying therapies (e.g., hydroxyurea, crizanlizumab, voxelotor) 8 weeks before the planned start of mobilization and conditioning [see Drug Interactions (7.2, 7.3)].

Sickle Cell Disease

Prior to apheresis it is recommended that patients be transfused with a goal to maintain hemoglobin S (HbS) levels < 30% of total hemoglobin (Hb) while keeping total Hb concentration ≤ 11 g/dL.

Transfusion-dependent β-thalassemia

Prior to apheresis procedure it is recommended that patients be transfused with a goal to maintain hemoglobin (Hb) ≥ 11 g/dL.

Mobilization and Apheresis

Patients are required to undergo CD34^+ HSC mobilization followed by apheresis to isolate the CD34^+ cells needed for CASGEVY manufacturing.

Plerixafor and Granulocyte-Colony Stimulating Factor (G-CSF) were used for mobilization in patients with TDT.

Single agent plerixafor was used for mobilization in patients with SCD. G-CSF should not be administered for mobilization in patients with SCD.

Refer to the prescribing information for the mobilization agent(s) prior to treatment. See Clinical Studies (14) for description of the mobilization regimen used in the clinical trials.

Maximize CD34^+ cell collection to obtain as many CD34^+ cells as possible for product manufacturing during each mobilization and apheresis cycle. Perform up to three consecutive days of cell collection for product manufacturing per cycle, if clinically tolerated. A total collection target of at least 20 × 10^6 CD34^+ cells/kg is recommended for product manufacture. Collected cells should be sent for product manufacturing even if the total collection target is not achieved. If the minimum dose of CASGEVY (3 × 10^6 CD34^+ cells/kg) is not met after initial product manufacturing, the patient will need to undergo additional cycles of mobilization and apheresis. Each mobilization and apheresis cycle must be separated by a minimum of 14 days.

An additional ≥ 2 × 10^6 CD34^+ cells/kg of unmodified back-up rescue cells must be collected from the patient and be cryopreserved prior to myeloablative conditioning and infusion with CASGEVY. The unmodified back-up cells may be needed for rescue treatment under any one of the following conditions: (1) compromise of CASGEVY after initiation of myeloablative conditioning and before CASGEVY infusion; (2) neutrophil engraftment failure; or (3) loss of engraftment after infusion with CASGEVY [see Warnings and Precautions (5.1)].

Myeloablative Conditioning

In patients with SCD it is recommended that patients be transfused at least 8 weeks prior to the initiation of myeloablative conditioning, with a goal of maintaining hemoglobin S (HbS) levels of < 30% of total Hb while keeping total Hb concentration ≤ 11 g/dL. At initiation of red blood cell exchange or simple transfusions, discontinue disease modifying therapies for sickle cell disease (e.g., hydroxyurea, crizanlizumab, voxelotor).

In patients with TDT it is recommended that patients be transfused to maintain hemoglobin (Hb) ≥ 11 g/dL for 60 days prior to myeloablative conditioning.

Stop iron chelation therapy at least 7 days prior to myeloablative conditioning.

Do not begin myeloablative conditioning until the complete set of vial(s) comprising the total dose of CASGEVY has been received and stored at the treatment center and the availability of the back-up collection of unmodified rescue cells is confirmed. See the Lot Information Sheet provided with the product shipment for confirmation of the total dose of CASGEVY.

Administer full myeloablative conditioning prior to treatment with CASGEVY ^1. Refer to the prescribing information for the myeloablative conditioning agent prior to treatment. See Clinical Studies (14) for the conditioning regimen used in the clinical trials.

Consider administration of anti-seizure prophylaxis. Use agents other than phenytoin prior to initiating busulfan conditioning. Consider prophylaxis for hepatic veno-occlusive disease (VOD)/hepatic sinusoidal obstruction syndrome prior to initiating busulfan conditioning.

CASGEVY must be administered between 48 hours and 7 days after the last dose of the myeloablative conditioning.

Receipt and Storage of CASGEVY

- CASGEVY is shipped to the treatment center frozen in a vapor phase of liquid nitrogen shipper.
- Confirm patient identifiers on the product label(s) and Lot Information Sheet.
- If there are any concerns about the product or packaging upon receipt, contact Vertex at +1-877-634-8789.
- Transfer CASGEVY from the vapor phase of nitrogen shipper to the treatment center vapor phase of liquid nitrogen storage at ≤ -135 °C (≤ -211 °F).

Preparing for CASGEVY Administration

CASGEVY contains human cells. Follow universal precautions (wearing gloves, protective clothing, and eye protection) and local biosafety guidelines applicable for handling and disposal of such products to avoid potential transmission of infectious diseases. All material that has been in contact with CASGEVY (solid and liquid waste) should be handled and disposed of as potentially infectious waste in accordance with local biosafety guidelines.

Coordinate the timing of CASGEVY thaw and infusion. Confirm the infusion time in advance and adjust the start time for thaw so that CASGEVY is available for infusion when the patient and healthcare providers are ready. Thaw and infuse one vial at a time.

Premedication: Administer an antipyretic (e.g., acetaminophen) and an antihistamine (e.g., diphenhydramine hydrochloride) prior to administering CASGEVY.

Before thaw, confirm CASGEVY is printed on the vial label and the patient's identity matches the unique patient information located on the CASGEVY vial(s). Do not infuse CASGEVY if the information on the patient-specific label on any of the vials does not match the intended patient, and contact Vertex at +1-877-634-8789.

A dose of CASGEVY may be contained in one or more cryopreserved patient-specific vial(s). Ensure that the correct number of vials are present. Use the accompanying Lot Information Sheet to confirm the total number of vials to be administered and confirm that each vial is within the expiration date prior to preparation of CASGEVY for infusion.

Inspect the vial(s) for any breaks or cracks prior to thawing. If a vial is compromised, do not infuse the contents. Call Vertex at +1-877-634-8789.

When the dose consists of multiple vials, thaw and administer one vial at a time. While thawing and administering a vial, remaining vials must remain in cryostorage at ≤ -135 °C (≤ -211 °F).

Assemble supplies needed to thaw and withdraw the product from the vial(s). With the exception of the water bath, these supplies are single use. Assemble sufficient supplies for each vial to be administered:

- Water bath
- Alcohol swabs
- Vial adapter (to allow for needleless extraction)
- 18-micron stainless steel filter
- 30 mL luer-lock syringe
- 0.9% sodium chloride (saline, 5 to 10 mL needed for each vial)
- 10 mL luer-lock syringe for saline rinse

Thawing the CASGEVY vials

- Thaw each CASGEVY vial at 37 °C (98 °F) using a water bath. Thaw each vial holding the vial neck, gently agitating clockwise and counterclockwise.
- Thawing of each vial can take between 10 to 15 minutes. Thawing is complete when ice crystals are no longer visible in the vial. Ensure water bath temperature does not exceed 40 °C (104 °F) during thawing.
- Do not leave CASGEVY unattended during thaw.
- Remove vial from water bath immediately once thawed.
- The thawed product should appear as a cellular suspension, which may contain proteinaceous particles or cellular aggregates.
- Inspect the vial(s) for any breaks or cracks after thawing.
- Do not wash, spin down and/or resuspend CASGEVY in new media prior to infusion.
- Do not sample, alter, irradiate, or refreeze CASGEVY.
- Infuse within 20 minutes of thaw.

2.3 Administration

CASGEVY is for autologous use only. Before infusion, confirm that the patient's identity matches the unique patient identifiers on the CASGEVY vial(s). Do not infuse CASGEVY if the information on the patient-specific label does not match the intended patient.

A patient's dose may consist of multiple vials. All vials must be administered. Use the Lot Information Sheet to confirm the total number of vials to be administered. The entire volume of each vial provided should be infused. If more than one vial is provided, administer each vial completely before proceeding to thaw and infuse the next vial.

1. Attaching the vial adapter and filter

a. Remove the flip-away tab of the vial cap; clean the septum with an alcohol swab.
b. Remove the cap on the vial adapter spike.
c. With the thumb and forefinger of both hands, push the adapter into the vial septum, applying equal pressure until there is a single pop.
d. Pull up on the adapter until you feel it lock.
e. Attach the filter to the vial adapter.

2. Withdrawing CASGEVY from the vial

a. Attach an empty 30 mL syringe to the filter.
b. Withdraw the entire vial product volume.
c. Remove the product-filled syringe from the filter and set aside.

d. Draw 5 - 10 mL of saline into the empty 10 mL syringe.
e. Attach the saline-filled syringe to the filter.
f. Inject the saline into the CASGEVY vial and remove the empty syringe from the filter. Discard the empty syringe.

g. Attach the product-filled syringe to the filter.
h. Withdraw the contents of the vial into the syringe, then remove the syringe from the filter.
i. Peel the product/patient identifier label from the Lot Information Sheet and affix to the product-filled syringe.

3. Administer CASGEVY through central venous catheter

a. Perform a two-person confirmation and verification of patient's identification at the bedside prior to the infusion of each vial(s).
b. Administer CASGEVY as an intravenous bolus (IV push) within 20 minutes of product thaw. Do not use an in-line blood filter or infusion pump when infusing CASGEVY. The total volume of CASGEVY administered within one hour must not exceed 2.6 mL/kg.
c. After administration of each vial of CASGEVY, flush the primary line with 0.9% sodium chloride solution, using enough volume to flush the tubing and the length of the IV catheter.

Repeat steps 1-3 for each remaining vial. If more than one vial is needed to achieve the patient-specific dose, administer each vial completely before proceeding to thaw and infuse the next vial.

After CASGEVY Administration

Follow standard procedures for patient management after HSC transplantation after CASGEVY infusion.

- Irradiate any blood products required within the first 3 months after CASGEVY infusion.
- Patients treated with CASGEVY should not donate blood, organs, tissues, or cells at any time in the future.
- Restarting iron chelation after CASGEVY infusion may be necessary and should be based on clinical practice. Avoid the use of non-myelosuppressive iron chelators for at least 3 months and use of myelosuppressive iron chelators for at least 6 months after CASGEVY infusion. Phlebotomy can be used in lieu of iron chelation, when appropriate [see Drug Interactions (7.4)].

3 DOSAGE FORMS AND STRENGTHS

CASGEVY is a cell suspension for intravenous infusion.

A single dose of CASGEVY is composed of one or more vials. Each vial contains 4 to 13 × 10^6 CD34^+ cells/mL suspended in 1.5 to 20 mL cryopreservation medium [see How Supplied/Storage and Handling (16)]. The minimum recommended dose of CASGEVY is 3 × 10^6 CD34^+ cells per kg of body weight.

See the Lot Information Sheet for actual strength and dose. The Lot Information Sheet is included inside the lid of the liquid nitrogen dry shipper used to transport CASGEVY.

4 CONTRAINDICATIONS

None.

5 WARNINGS AND PRECAUTIONS

5.1 Neutrophil Engraftment Failure

There is potential risk of neutrophil engraftment failure after treatment with CASGEVY. In the clinical trials, all treated patients achieved neutrophil engraftment and no patients received rescue CD34^+ cells.

Monitor absolute neutrophil counts (ANC) and manage infections according to standard guidelines and medical judgement. In the event of neutrophil engraftment failure, patients should be infused with rescue CD34^+ cells [see Adverse Reactions (6.1)].

5.2 Delayed Platelet Engraftment

Delayed platelet engraftment has been observed with CASGEVY treatment. There is an increased risk of bleeding until platelet engraftment is achieved [see Adverse Reactions (6.1)]. In the clinical trials, there was no association observed between incidence of bleeding events and time to platelet engraftment.

Monitor patients for bleeding according to standard guidelines and medical judgement. Conduct frequent platelet counts until platelet engraftment and platelet recovery are achieved. Perform blood cell count determination and other appropriate testing whenever clinical symptoms suggestive of bleeding arise.

5.3 Hypersensitivity Reactions

Hypersensitivity reactions, including anaphylaxis, can occur due to dimethyl sulfoxide (DMSO) or dextran 40 in the cryopreservation solution. Monitor patients for hypersensitivity reactions during and after infusion.

5.4 Off-Target Genome Editing Risk

The risk of unintended, off-target editing in an individual's CD34^+ cells cannot be ruled out due to genetic variants. The clinical significance of potential off-target editing is unknown.

6 ADVERSE REACTIONS

6.1 Clinical Trials Experience

Because clinical trials are conducted under widely varying conditions, adverse reaction rates observed in the clinical trials of a drug cannot be directly compared to rates in the clinical trials of another drug and may not reflect the rates observed in practice.

The most common Grade 3 or 4 non-laboratory adverse reactions (occurring in ≥ 25%) were mucositis and febrile neutropenia in patients with SCD and patients with TDT, and decreased appetite in patients with SCD.

All (100%) of the patients with TDT and SCD experienced Grade 3 or 4 neutropenia and thrombocytopenia. Other common Grade 3 or 4 laboratory abnormalities (≥ 50%) include leukopenia, anemia and lymphopenia.

Sickle Cell Disease

The safety of CASGEVY in patients with SCD was evaluated in an open-label, single-arm trial (Trial 1) and a long-term follow-up trial (Trial 3), in which 44 adolescent and adult patients with SCD were treated with CASGEVY after undergoing myeloablative conditioning with busulfan. The adverse event profile was generally consistent with that expected from busulfan myeloablative conditioning and HSC transplant.

The median (min, max) duration of follow-up for 44 patients with SCD after being administered CASGEVY was 19.3 (0.8, 48.1) months.

Serious adverse reactions after myeloablative conditioning and CASGEVY infusion were observed in 45% of patients with SCD. The most common serious adverse reactions (≥ 2 patients) were cholelithiasis, pneumonia, abdominal pain, constipation, pyrexia, abdominal pain upper, non-cardiac chest pain, oropharyngeal pain, pain, and sepsis. One (2%) patient died due to a COVID-19 infection and subsequent respiratory failure. The event was not related to CASGEVY.

Table 1 presents the Grade 3 or 4 non-laboratory adverse reactions observed after myeloablative conditioning and CASGEVY infusion in at least 10% of patients in Trial 1. Table 2 presents the Grade 3 or 4 laboratory abnormalities that occurred in at least 10% of patients with SCD.

Table 1: Grade 3 or 4 non-laboratory adverse reactions in ≥ 10% of patients with SCD who underwent busulfan myeloablative conditioning and received CASGEVY in Trial 1: Day 1 to Month 24 after CASGEVY infusion [Table includes adverse events associated with busulfan myeloablative conditioning and treatment with CASGEVY. Adverse event profile generally consistent with that expected from busulfan myeloablative conditioning and HSC transplant.]
System organ class, preferred term | Patients with SCD (Trial 1) (N=44) n (%)
Blood and lymphatic system disorders
Febrile neutropenia | 21 (48)
Gastrointestinal disorders
Mucositis [Mucositis includes mucosal inflammation, pharyngeal inflammation, and stomatitis.] , [Encompasses preferred terms that belong to other system organ class.] | 38 (86)
Abdominal pain [Abdominal pain includes abdominal pain and abdominal pain upper.] | 5 (11)
Hepatobiliary disorders
Cholelithiasis | 5 (11)
Metabolism and nutrition disorders
Decreased appetite | 18 (41)
Musculoskeletal and connective tissue disorders
Musculoskeletal pain [Musculoskeletal pain includes back pain, musculoskeletal chest pain, neck pain, non-cardiac chest pain, and pain in extremity.] , | 6 (14)
Skin and subcutaneous tissue disorders
Pruritus | 5 (11)

Other clinically important adverse reactions that occurred in less than 10% of patients or were Grade 1 or Grade 2 include the following:

Hepatobiliary disorders: Veno-occlusive liver disease (1 [2%] patient).

Infusion-related reactions: 6 (14%) patients, including preferred terms of abdominal pain in 3 (7%) patients; and infusion-related reaction, nausea, non-cardiac chest pain, pruritus, sinus tachycardia, and vomiting in 1 (2%) patient each.

Table 2: Grade 3 or 4 laboratory abnormalities in ≥ 10% of patients with SCD who underwent busulfan myeloablative conditioning and received CASGEVY in Trial 1: Day 1 to Month 24 after CASGEVY infusion [Table includes laboratory abnormalities associated with busulfan myeloablative conditioning and treatment with CASGEVY. Laboratory abnormalities were generally consistent with those expected from busulfan myeloablative conditioning and HSC transplant.]
Laboratory abnormality | Patients with SCD (Trial 1) N=44 [The denominator for CD4 lymphocytes decreased is 43 and the denominator for all other laboratory data is 44, based on evaluable data at the time of the interim analysis.] (%)
Neutropenia | 100
Thrombocytopenia | 100
Leukopenia | 98
Anemia | 84
Lymphopenia | 50
CD4 lymphocytes decreased | 23
Activated partial thromboplastin time prolonged | 16
Hyperbilirubinemia | 14

Platelet engraftment

Platelet engraftment in patients with SCD is defined as 3 consecutive measurements of platelet counts ≥ 50 × 10^9/L, obtained on 3 different days after CASGEVY infusion, without administration of platelet transfusions for 7 days. In Trial 1, the median (min, max) time to platelet engraftment was 35 (23, 126) days (n=43). There was no association observed between bleeding events and time to platelet engraftment.

Neutrophil engraftment

Neutrophil engraftment is defined as 3 consecutive measurements of ANC ≥ 500 cells/µL on 3 different days after CASGEVY infusion, without use of the unmodified rescue CD34^+ cells. In Trial 1, the median (min, max) time to neutrophil engraftment was 27 (15, 40) days (n=44). There was no association observed between infections and time to neutrophil engraftment. There was no use of rescue CD34^+ cells in any patient.

Transfusion-dependent β-thalassemia

The safety of CASGEVY in patients with TDT was evaluated in an open-label, single-arm trial (Trial 2) and a long-term follow-up trial (Trial 3), in which 52 adolescent and adult patients with TDT were treated with CASGEVY after undergoing myeloablative conditioning with busulfan. The adverse event profile was generally consistent with that expected from busulfan myeloablative conditioning and HSC transplant.

The median (min, max) duration of follow-up for 52 patients with TDT after being administered CASGEVY was 20.4 (2.1, 48.1) months.

Serious adverse reactions after myeloablative conditioning and CASGEVY infusion were observed in 33% of patients with TDT. The most common serious adverse reactions (≥ 2 patients) were veno-occlusive liver disease, pneumonia, hypoxia, thrombocytopenia, viral infection, and upper respiratory tract infection.

Table 3 presents the Grade 3 or 4 non-laboratory adverse reactions observed after myeloablative conditioning and CASGEVY infusion in at least 10% of patients in Trial 2. Table 4 presents the Grade 3 or 4 laboratory abnormalities that occurred in at least 10% of patients with TDT.

Table 3: Grade 3 or 4 non-laboratory adverse reactions in ≥ 10% of patients with TDT who underwent busulfan myeloablative conditioning and received CASGEVY in Trial 2: Day 1 to Month 24 after CASGEVY infusion [Table includes adverse events associated with busulfan myeloablative conditioning and treatment with CASGEVY. Adverse event profile generally consistent with that expected from busulfan myeloablative conditioning and HSC transplant.]
System organ class, preferred term | Patients with TDT (Trial 2) (N=52) n (%)
Blood and lymphatic system disorders
Febrile neutropenia | 28 (54)
Gastrointestinal disorders
Mucositis [Mucositis includes anal inflammation, mucosal inflammation, pharyngeal inflammation, and stomatitis.] , [Encompasses preferred terms that belong to other system organ class.] | 37 (71)
Hepatobiliary disorders
Veno-occlusive liver disease | 5 (10)
Metabolism and nutrition disorders
Decreased appetite | 12 (23)
Respiratory, thoracic and mediastinal disorders
Epistaxis | 7 (13)

Other clinically important adverse reactions that occurred in less than 10% of patients or were Grade 1 or Grade 2 include the following:

Immune system disorders: Hemophagocytic lymphohistiocytosis (1 [2%] patient).

Nervous system disorders: Cerebellar hemorrhage (intracranial hemorrhage) (1 [2%] patient).

Infusion-related reactions: 12 (23%) patients, including preferred terms of abdominal pain and nausea in 4 (8%) patients each; pruritus and vomiting in 2 (4%) patients each; and abdominal pain lower, chills, sinus tachycardia, and tachycardia in 1 (2%) patient each.

Table 4: Grade 3 or 4 laboratory abnormalities in ≥ 10% of patients with TDT who underwent busulfan myeloablative conditioning and received CASGEVY in Trial 2: Day 1 to Month 24 after CASGEVY infusion [Table includes laboratory abnormalities associated with busulfan myeloablative conditioning and treatment with CASGEVY. Laboratory abnormalities were generally consistent with those expected from busulfan myeloablative conditioning and HSC transplant.]
Laboratory abnormality | Patients with TDT (Trial 2) N=52 [The denominator for CD4 lymphocytes decreased is 48 and the denominator for all other laboratory data is 52, based on evaluable data at the time of the interim analysis.] (%)
Neutropenia | 100
Thrombocytopenia | 100
Leukopenia | 98
Anemia | 92
Lymphopenia | 79
CD4 lymphocytes decreased | 23
Hyperbilirubinemia | 23
Alanine aminotransferase increased | 19
Hypokalemia | 19
Gamma-glutamyltransferase increased | 17
Activated partial thromboplastin time prolonged | 13
Hypocalcemia | 12

Platelet engraftment

Platelet engraftment in patients with TDT is defined as 3 consecutive measurements of platelet counts ≥ 20 × 10^9/L, obtained on 3 different days after CASGEVY infusion, without administration of platelet transfusions for 7 days. In Trial 2, the median (min, max) time to platelet engraftment was 44 (20, 200) days (n=52). There is an increased risk of bleeding until platelet engraftment is achieved. In the clinical trials, there was no association observed between incidence of bleeding events and time to platelet engraftment. Patients without a spleen had an earlier median time to platelet engraftment than patients with an intact spleen. Median (min, max) time to platelet engraftment was 34.5 (20, 78) days in patients without a spleen and 47.5 (27, 200) days in patients with an intact spleen. While the use of thrombopoietin (TPO) mimetics was not specified in the trial protocol, five patients (10%) received a TPO mimetic at the time of platelet engraftment. All 5 patients continued TPO mimetic use for thrombocytopenia beyond engraftment. The total duration of TPO mimetic use was 98-457 days.

Neutrophil engraftment

Neutrophil engraftment is defined as 3 consecutive measurements of absolute neutrophil count (ANC) ≥ 500 cells/µL on 3 different days after CASGEVY infusion, without use of the unmodified rescue CD34^+ cells. In Trial 2, the median (min, max) time to neutrophil engraftment was 29 (12, 56) days (n=52). There was no association observed between infections and time to neutrophil engraftment. One patient had neutrophil engraftment on Day 56. There was no use of rescue CD34^+ cells in any patient.

7 DRUG INTERACTIONS

No formal drug interaction studies have been performed. CASGEVY is not expected to interact with the hepatic cytochrome P-450 family of enzymes or drug transporters.

7.1 Use of Granulocyte-Colony Stimulating Factor (G-CSF)

Granulocyte-Colony Stimulating Factor (G-CSF) must not be used for CD34^+ HSC mobilization of patients with SCD.

7.2 Use of Hydroxyurea

Discontinue the use of hydroxyurea at least 8 weeks prior to start of each mobilization cycle and conditioning. There is no experience of the use of hydroxyurea after CASGEVY infusion.

7.3 Use of Voxelotor and Crizanlizumab

Discontinue the use of voxelotor and crizanlizumab at least 8 weeks prior to start of mobilization and conditioning, as their interaction potential with mobilization and myeloablative conditioning agents is not known.

7.4 Use of Iron Chelators

Discontinue the use of iron chelators at least 7 days prior to initiation of myeloablative conditioning, due to potential interaction with the conditioning agent. Some iron chelators are myelosuppressive. If iron chelation is required, avoid the use of non-myelosuppressive iron chelators for at least 3 months and use of myelosuppressive iron chelators for at least 6 months after CASGEVY infusion. Phlebotomy can be used instead of iron chelation, when appropriate.

7.5 Live Vaccines

The safety of immunization with live viral vaccines during or following CASGEVY treatment has not been studied.

8 USE IN SPECIFIC POPULATIONS

Consider the risks of mobilization and myeloablative conditioning agents in patients with reproductive potential and patients that are pregnant or breastfeeding.

8.1 Pregnancy

Risk Summary

There are no clinical data from the use of exagamglogene autotemcel in pregnant women. No animal reproductive and developmental toxicity studies have been conducted with exagamglogene autotemcel to assess whether it can cause fetal harm when administered to a pregnant woman. CASGEVY must not be administered during pregnancy because of the risks associated with myeloablative conditioning. Pregnancy after CASGEVY infusion should be discussed with the treating physician.

In the U.S. general population, the estimated background risk of major birth defects and miscarriage in clinically recognized pregnancies is 2-4% and 15-20%, respectively.

8.2 Lactation

Risk Summary

There are no data on the presence of exagamglogene autotemcel in human or animal milk, the effects on the breastfed child, or the effects on milk production. Because of the potential risks associated with myeloablative conditioning, breastfeeding should be discontinued during conditioning. The developmental and health benefits of breastfeeding should be considered along with the mother's clinical need for CASGEVY and any potential adverse effects on the breastfed child from CASGEVY or from the underlying maternal condition. Breastfeeding after CASGEVY infusion should be discussed with the treating physician.

8.3 Females and Males of Reproductive Potential

Pregnancy Testing

A negative serum pregnancy test must be confirmed prior to the start of each mobilization cycle and re-confirmed prior to myeloablative conditioning.

Contraception

There are insufficient exposure data to provide a precise recommendation on duration of contraception following treatment with CASGEVY. Women of childbearing potential and men capable of fathering a child should use effective method of contraception from start of mobilization through at least 6 months after administration of CASGEVY. Advise patients of the risks associated with conditioning agents.

Infertility

There are no data on the effects of exagamglogene autotemcel on human fertility. Effects on male and female fertility have not been evaluated in animal studies. Infertility has been observed with myeloablative conditioning therefore, advise patients of fertility preservation options before treatment, if appropriate.

8.4 Pediatric Use

The safety and efficacy of CASGEVY has been established in pediatric patients with SCD and TDT aged 12 years and older. Use of CASGEVY in patients aged 12 to less than 18 years is supported by data in 12 patients with SCD in Trial 1 (6 patients evaluable for the primary efficacy analysis), and 18 patients with TDT in Trial 2 (11 patients evaluable for the primary efficacy analysis). The efficacy and safety profile of CASGEVY in pediatric patients aged 12 years and older were consistent with the efficacy and safety in adult patients [see Adverse Reactions (6.1) and Clinical Studies (14.1, 14.2)].

Patients with SCD

The median (min, max) time to platelet engraftment was 45 (23, 81) days in pediatric patients aged 12 years and older and 32 (23, 126) days in adult patients. The median (min, max) time to neutrophil engraftment was 28 (24, 40) days in pediatric patients aged 12 years and older and 26 (15, 38) days in adult patients.

Patients with TDT

The median (min, max) time to platelet engraftment was 45 (20, 199) days in pediatric patients aged 12 years and older and 41.5 (24, 200) days in adult patients. The median (min, max) time to neutrophil engraftment was 30 (19, 56) days in pediatric patients aged 12 years and older and 28.5 (12, 40) days in adult patients.

The safety and efficacy of CASGEVY in pediatric patients aged less than 12 years has not been established.

8.5 Geriatric Use

CASGEVY has not been studied in patients > 65 years of age. HSC transplantation must be appropriate for a patient to be treated with CASGEVY.

8.6 Patients with Renal Impairment

CASGEVY has not been studied in patients with renal impairment, defined as estimated glomerular filtration rate < 60 mL/min/1.73 m^2. Patients should be assessed for renal impairment to ensure HSC transplantation is appropriate.

8.7 Patients with Hepatic Impairment

CASGEVY has not been studied in patients with hepatic impairment. Patients should be assessed for hepatic impairment to ensure HSC transplantation is appropriate.

8.8 Patients Seropositive for Human Immunodeficiency Virus (HIV), Hepatitis B Virus (HBV) or Hepatitis C Virus (HCV)

CASGEVY has not been studied in patients with HIV-1, HIV-2, HBV or HCV. Perform screening for HIV-1, HIV-2, HBV and HCV and any other infectious agents in accordance with local guidelines before collection of cells for manufacturing. CASGEVY should not be used in patients with active HIV-1, HIV-2, HBV or HCV.

8.9 Patients with Prior HSC Transplant

CASGEVY has not been studied in patients who have received a prior allogeneic or autologous HSC transplant. Treatment with CASGEVY is not recommended in these patients.

11 DESCRIPTION

CASGEVY (exagamglogene autotemcel) is a cellular gene therapy consisting of autologous CD34^+ HSCs edited by CRISPR/Cas9-technology at the erythroid specific enhancer region of the BCL11A gene to reduce BCL11A expression in erythroid lineage cells, leading to increased fetal hemoglobin (HbF) protein production.

CASGEVY is prepared from the patient's own HSCs, which are obtained via apheresis procedure(s). The autologous cells are enriched for CD34^+ cells, and then genome edited ex vivo by introducing the CRISPR/Cas9 ribonucleoprotein (RNP) complex by electroporation. The guide RNA included in the RNP complex enables CRISPR/Cas9 to make a precise DNA double-strand break at a critical transcription factor binding site (GATA1) in the erythroid specific enhancer region of the BCL11A gene. As a result of the editing, GATA1 binding is disrupted and BCL11A expression is reduced. This reduction in BCL11A expression conversely results in an increase in gamma-globin expression and downstream fetal hemoglobin formation.

The edited CD34^+ cells are formulated into a suspension in a sterile cryopreservation medium and cryopreserved. CASGEVY is shipped as a frozen suspension in patient-specific vial(s). The product is thawed prior to infusion and administered as a HSC transplant [see Dosage and Administration (2.2) and How Supplied/Storage and Handling (16)]. Due to the presence of cells, the thawed product may be clear to slightly cloudy and may contain small inherent proteinaceous particles or visible cell aggregates.

The formulation contains 5% dimethyl sulfoxide (DMSO) and dextran 40.

12 CLINICAL PHARMACOLOGY

12.1 Mechanism of Action

After CASGEVY infusion, the edited CD34^+ cells engraft in the bone marrow and differentiate to erythroid lineage cells with reduced BCL11A expression. Reduced BCL11A expression results in an increase in γ-globin expression and HbF protein production in erythroid cells. In patients with severe sickle cell disease, HbF expression reduces intracellular hemoglobin S (HbS) concentration, preventing the red blood cells from sickling and addressing the underlying cause of disease, thereby eliminating VOCs. In patients with transfusion-dependent β-thalassemia, γ-globin production improves the α-globin to non-α-globin imbalance thereby reducing ineffective erythropoiesis and hemolysis and increasing total hemoglobin levels, addressing the underlying cause of disease, and eliminating the dependence on regular red blood cell (RBC) transfusions.

12.2 Pharmacodynamics

Sickle Cell Disease

Fetal Hemoglobin and Total Hemoglobin

HbF and total Hb over time are provided in Table 5 for all patients administered CASGEVY for the treatment of sickle cell disease (full analysis set). HbF and total Hb over time for the subset of patients included in the primary efficacy analysis were consistent with full analysis set.

Table 5: Proportion of hemoglobin comprised by HbF (%) and total Hb (g/dL) over time in patients with SCD in Trial 1
 | CASGEVY Full Analysis Set (FAS) (N=44)
 | Proportion of total Hb comprised by HbF (%) [%HbF/Hb data not available for all patients at all timepoints.] | Total Hb (g/dL)
Month 3
n | 43 | 43
Mean (SD) | 36.9 (9.0) | 11.9 (1.5)
Median (min, max) | 36.2 (17.8, 59.6) | 11.9 (8.2, 15.4)
Month 6
n | 38 | 38
Mean (SD) | 43.9 (8.6) | 12.5 (1.8)
Median (min, max) | 44.3 (14.9, 68.4) | 12.3 (7.2, 15.9)
Month 12
n | 32 | 31
Mean (SD) | 43.4 (4.6) | 13.0 (1.5)
Median (min, max) | 42.9 (35.1, 52.1) | 12.9 (10.3, 15.7)
Month 18
n | 27 | 27
Mean (SD) | 42.3 (5.8) | 13.3 (1.9)
Median (min, max) | 43.1 (27.5, 53.3) | 12.7 (11.0, 17.3)
Month 24
n | 17 | 17
Mean (SD) | 42.1 (5.2) | 13.1 (1.8)
Median (min, max) | 42.2 (33.3, 49.1) | 13.0 (10.5, 17.3)
SD: Standard Deviation.

The mean (SD) proportion of Hb comprised by HbF was 43.9% (8.6%) at Month 6 and was maintained thereafter. Increases in mean (SD) total Hb levels were observed as early as Month 3 after CASGEVY infusion, continued to increase to 12.5 (1.8) g/dL at Month 6, and was maintained thereafter. Of the 44 patients infused with CASGEVY, three male patients reached total Hb levels of at least 16.5 g/dL at one or more time points after Month 9.

Consistent with the increase in HbF levels, the mean (SD) proportion of circulating erythrocytes expressing HbF (F-cells) at Month 3 was 70.1% (13.8%) and continued to increase over time to 94.0% (12.4%) at Month 6, with levels remaining stable thereafter, indicating sustained pan-cellular expression of HbF.

Proportion of Alleles with Intended Genetic Modification

The mean (SD) proportion of alleles with intended genetic modification in the bone marrow and in peripheral blood is shown in Table 6 for all patients administered CASGEVY for the treatment of sickle cell disease in Trial 1.

Table 6: Proportion of alleles with intended genetic modification over time in patients with SCD in Trial 1
 | CASGEVY Full Analysis Set (FAS) (N=44)
 | Proportion of Alleles with Intended Genetic Modification in CD34^+ Cells in Bone Marrow [Allelic editing data not available for all patients at all timepoints. Allelic editing in bone marrow was first assessed at Month 6.] | Proportion of Alleles with Intended Genetic Modification in Peripheral Blood
Month 1
n | -- | 42
Mean (SD) |  | 53.5 (18.2)
Month 3
n | -- | 42
Mean (SD) |  | 70.8 (10.6)
Month 6
n | 37 | 38
Mean (SD) | 86.1 (7.5) | 73.4 (8.1)
Month 12
n | 31 | 31
Mean (SD) | 86.1 (8.6) | 74.2 (8.7)
Month 24
n | 16 | 17
Mean (SD) | 88.5 (4.6) | 79.2 (5.6)

Subgroup analyses evaluating the effects of age (adolescent versus adult) and sex (male versus female) showed consistent results on total hemoglobin, fetal hemoglobin and allelic editing in patients with SCD.

Transfusion-dependent β-thalassemia

Fetal Hemoglobin and Total Hemoglobin

Total Hb and HbF levels over time are provided in Table 7 for all patients administered CASGEVY for the treatment of transfusion-dependent β-thalassemia (full analysis set). HbF and total Hb over time for the subset of patients included in the primary efficacy analysis were consistent with full analysis set.

Table 7: Total Hb (g/dL) and HbF levels over time in patients with TDT in Trial 2
 | CASGEVY Full Analysis Set (FAS) (N=52)
 | Total Hb (g/dL) [Hb/HbF data not available for all patients at all timepoints.] | Total HbF (g/dL)
Month 3
n | 47 | 46
Mean (SD) | 11.4 (2.2) | 7.7 (2.9)
Median (min, max) | 11.5 (7.1, 17.6) | 8.4 (0.3, 13.0)
Month 6
n | 45 | 45
Mean (SD) | 12.2 (2.0) | 10.9 (2.8)
Median (min, max) | 12.5 (6.5, 16.4) | 11.6 (1.1, 14.5)
Month 12
n | 43 | 42
Mean (SD) | 12.8 (2.1) | 11.5 (2.5)
Median (min, max) | 12.9 (6.2, 17.2) | 12.3 (4.4, 15.3)
Month 18
n | 30 | 27
Mean (SD) | 12.9 (2.1) | 11.5 (2.4)
Median (min, max) | 13.1 (6.5, 17.7) | 12.0 (4.3, 15.0)
Month 24
n | 15 | 15
Mean (SD) | 13.2 (2.1) | 11.9 (2.5)
Median (min, max) | 13.5 (10.1, 16.9) | 12.1 (6.7, 15.4)

Increases in mean (SD) total Hb and HbF levels were observed as early as Month 3 after CASGEVY infusion and continued to increase to 12.2 (2.0) g/dL and 10.9 (2.8) g/dL respectively at Month 6. After Month 6, levels of total Hb and HbF were maintained thereafter, with HbF comprising ≥ 88% of total Hb.

Consistent with the increase in HbF levels, the mean (SD) proportion of circulating erythrocytes expressing HbF (F-cells) at Month 3 was 73.8% (19.7%) and continued to increase over time to 95.9% (15.2%) at Month 6, with levels remaining stable from thereafter, indicating sustained pan-cellular expression of HbF.

Proportion of Alleles with Intended Genetic Modification

The mean (SD) proportion of alleles with intended genetic modification in the bone marrow and in peripheral blood is shown in Table 8 for all patients administered CASGEVY for the treatment of transfusion-dependent β-thalassemia in Trial 2.

Table 8: Proportion of alleles with intended genetic modification over time in patients with TDT in Trial 2
 | CASGEVY Full Analysis Set (FAS) (N=52)
 | Proportion of Alleles with Intended Genetic Modification in CD34^+ Cells in Bone Marrow [Allelic editing data not available for all patients at all timepoints. Allelic editing in bone marrow was first assessed at Month 6.] | Proportion of Alleles with Intended Genetic Modification in Peripheral Blood
Month 1
n | -- | 46
Mean (SD) |  | 50.2 (20.6)
Month 3
n | -- | 46
Mean (SD) |  | 66.2 (11.4)
Month 6
n | 41 | 44
Mean (SD) | 78.0 (82.3) | 66.7 (11.3)
Month 12
n | 41 | 43
Mean (SD) | 78.7 (12.6) | 67.7 (10.2)
Month 24
n | 13 | 15
Mean (SD) | 75.4 (16.4) | 65.3 (12.6)

Subgroup analyses evaluating the effects of age (adolescent versus adult), sex (male versus female), race, and genotype showed consistent results on total hemoglobin, fetal hemoglobin, and allelic editing in patients with TDT.

12.3 Pharmacokinetics

CASGEVY is an autologous cellular therapy which includes CD34^+ cells that have been edited ex vivo. The nature of CASGEVY is such that conventional studies on pharmacokinetics, absorption, distribution, metabolism, and elimination are not applicable.

13 NONCLINICAL TOXICOLOGY

13.1 Carcinogenesis, Mutagenesis, Impairment of Fertility

Conventional mutagenicity and carcinogenicity studies have not been conducted for CASGEVY. No studies on the effects of CASGEVY on fertility have been conducted.

14 CLINICAL STUDIES

14.1 Sickle Cell Disease

Trial 1 (NCT03745287) is an ongoing single-arm, multi-center trial evaluating the safety and efficacy of a single dose of CASGEVY in adult and adolescent patients with sickle cell disease. Eligible patients underwent mobilization and apheresis to collect CD34^+ stem cells for CASGEVY manufacture, followed by myeloablative conditioning and infusion of CASGEVY. Patients were then followed in Trial 1 for 24 months after CASGEVY infusion. Patients who complete or discontinue from Trial 1 are encouraged to enroll in Trial 3 (NCT04208529), an ongoing long-term follow-up trial for additional follow-up for a total of 15 years after CASGEVY infusion.

Patients were eligible for the trial if they had a history of at least 2 protocol-defined severe vaso-occlusive crisis (VOC) events during each of the 2 years prior to screening. In this trial severe VOC is defined as an occurrence of at least one of the following events:

- Acute pain event requiring a visit to a medical facility and administration of pain medications (opioids or intravenous [IV] non-steroidal anti-inflammatory drugs [NSAIDs]) or RBC transfusions
- Acute chest syndrome
- Priapism lasting > 2 hours and requiring a visit to a medical facility
- Splenic sequestration.

Patients were excluded if they had advanced liver disease, history of untreated Moyamoya disease, or presence of Moyamoya disease that in the opinion of the investigator put the patient at risk of bleeding. Patients aged 12 to 16 years were required to have normal transcranial doppler (TCD), and patients aged 12 to 18 years were excluded if they had any history of abnormal TCD in the middle cerebral artery and the internal carotid artery. Patients with an available 10/10 human leukocyte antigen matched related hematopoietic stem cell donor were excluded. Patients with more than 10 unplanned hospitalizations or emergency department visits related to chronic pain rather than SCD-related acute pain crises in the year before screening were excluded.

At the time of the interim analysis, a total of 63 patients enrolled in the trial, of which 58 (92%) patients started mobilization. A total of 44 (76%) patients received CASGEVY infusion and formed the full analysis set (FAS). Thirty-one patients from the FAS (70%) had adequate follow-up to allow evaluation of the primary efficacy endpoint and formed the primary efficacy set (PES). The key demographics and baseline characteristics for all patients administered CASGEVY in Trial 1 are shown in Table 9 below. The baseline characteristics and demographics are consistent between the PES and the FAS.

Table 9: Demographics and baseline characteristics of patients treated with CASGEVY at the interim analysis in Trial 1
Demographics and disease characteristics | Full Analysis Set (FAS) [Interim analysis conducted based on June 2023 data cut-off date.] (N=44) | Primary Efficacy Set (PES) , [The primary efficacy set (PES), is a subset of the full analysis set (FAS). The PES was defined as all patients who had been followed for at least 16 months after CASGEVY infusion. Patients who had less than 16 months follow-up due to death or discontinuation due to CASGEVY-related adverse events, or continuously received RBC transfusions for more than 10 months after CASGEVY were also included in this set. An additional patient who had less than 16 months of follow-up but was otherwise determined to be a non-responder for the primary efficacy endpoint, was also included in PES.] (N=31)
Age, n (%)
Adults (≥ 18 and ≤ 35 years) | 32 (73) | 24 (77)
Adolescents (≥ 12 and < 18 years) | 12 (27) | 7 (23)
All ages (≥ 12 and ≤ 35 years)
Median (min, max) | 20 (12, 34) | 21 (12, 34)
Sex, n (%)
Female | 20 (45) | 14 (45)
Male | 24 (55) | 17 (55)
Race, n (%)
Black or African American | 38 (86) | 27 (87)
White | 3 (7) | 1 (3)
Other | 3 (7) | 3 (10)
Genotype, n (%)
βS/βS | 40 (91) | 30 (97)
βS/β^0 | 3 (7) | 1 (3)
βS/β^+ | 1 (2) | 0
Annualized rate of severe VOCs in the 2 years prior to enrollment (events/year)
Median (min, max) | 3.5 (2.0, 18.5) | 3.5 (2.0, 18.5)
Annualized rate of hospitalizations due to severe VOCs in the 2 years prior to enrollment (events/year)
Median (min, max) | 2.5 (0.5, 9.5) | 2.0 (0.5, 8.5)

Mobilization and Apheresis

Patients underwent RBC exchange or simple transfusions for a minimum of 8 weeks before the planned start of mobilization and continued receiving transfusions or RBC exchanges until the initiation of myeloablative conditioning. Hemoglobin S (HbS) levels were maintained at < 30% of total Hb while keeping total Hb concentration ≤ 11 g/dL.

To mobilize stem cells for apheresis, patients in Trial 1 were administered plerixafor at a planned dose of 0.24 mg/kg via subcutaneous injection approximately 2 to 3 hours prior to each planned apheresis. Apheresis was carried out for up to 3 consecutive days to achieve the target collection of cells for manufacture and for the unmodified rescue CD34^+ cells.

The mean (SD) and median (min, max) number of mobilization and apheresis cycles required for the manufacture of CASGEVY and for the back-up collection of rescue CD34^+ cells were 2.3 (1.41) and 2 (1, 6), respectively. Six (10%) patients were unable to receive CASGEVY therapy due to not achieving the minimum dose.

Pre-treatment Conditioning

All patients received full myeloablative conditioning with busulfan prior to treatment with CASGEVY. Busulfan was administered for 4 consecutive days intravenously (IV) via a central venous catheter at a planned starting dose of 3.2 mg/kg/day once daily (qd) or 0.8 mg/kg every 6 hours (q6h). Busulfan plasma levels were measured by serial blood sampling and the dose adjusted to maintain exposure in the target range.

For the once daily dosing, four-day target cumulative busulfan exposure was 82 mg*h/L (range: 74 to 90 mg*h/L), corresponding to AUC0-24h of 5000 µM*min (range: 4500 to 5500 µM*min). For the every 6 hours dosing, the four-day target cumulative busulfan exposure was 74 mg*h/L (range: 59 to 89 mg*h/L), corresponding to AUC0-6h of 1125 µM*min (range: 900 to 1350 µM*min).

All patients received anti-seizure prophylaxis with agents other than phenytoin prior to initiating busulfan conditioning. Phenytoin was not used for anti-seizure prophylaxis because of its induction of cytochrome P-450 and resultant increased clearance of busulfan.

Prophylaxis for hepatic veno-occlusive disease (VOD)/hepatic sinusoidal obstruction syndrome was administered, per regional and institutional guidelines.

CASGEVY Administration

Patients were administered CASGEVY with a median (min, max) dose of 4.0 (2.9, 14.4) × 10^6 CD34^+ cells/kg as an IV infusion.

All patients were administered an antihistamine and an antipyretic prior to CASGEVY infusion.

After CASGEVY Administration

G-CSF was not recommended within the first 21 days after CASGEVY infusion.

As CASGEVY is an autologous therapy, immunosuppressive agents were not required after initial myeloablative conditioning.

Efficacy Results

An interim analysis (IA) was conducted with 31 patients eligible for the primary efficacy analysis, i.e., the primary efficacy set (PES). The median (min, max) total duration of follow-up was 26.0 (17.8, 48.1) months from the time of CASGEVY infusion in PES. There were no cases of graft failure or graft rejection.

The primary efficacy outcome was the proportion of VF12 responders, defined as patients who did not experience any protocol-defined severe VOCs for at least 12 consecutive months within the first 24 months after CASGEVY infusion in Trial 1. The proportion of patients who did not require hospitalization due to severe VOCs for at least 12 consecutive months within the 24-month evaluation period (HF12) was also assessed. The evaluation of VF12 and HF12 began 60 days after the last RBC transfusion for post-transplant support or SCD management. The median (min, max) time to the last RBC transfusion was 19 (11, 52) days following CASGEVY infusion for patients in the primary efficacy set.

The interim analysis occurred at the time when the alpha spending was approximately 0.02 for a one-sided test, when 31 patients were evaluable for VF12 responder status. The VF12 response rate was 29/31 (93.5%, 98% one-sided CI: 77.9%, 100.0%). The 29 VF12 responders did not experience protocol-defined severe VOCs during the evaluation period with a median duration of 22.2 months at the time of the interim analysis. One VF12 responder, after initially achieving a VF12 response, experienced an acute pain episode meeting the definition of a severe VOC at Month 22.8 requiring a 5-day hospitalization; this patient was reported to have a parvovirus B19 infection at the time. Of the 31 patients evaluable for VF12 response, one patient was not evaluable for HF12 response; the remaining 30 patients (100%, 98% one-sided CI: 87.8%, 100.0%) achieved the endpoint of HF12.

14.2 Transfusion-dependent β-thalassemia

Trial 2 (NCT03655678) is an ongoing open-label, multi-center, single-arm trial to evaluate the safety and efficacy of CASGEVY in adult and adolescent patients with transfusion-dependent β-thalassemia. Eligible patients underwent mobilization and apheresis to collect CD34^+ stem cells for CASGEVY manufacture, followed by myeloablative conditioning and infusion of CASGEVY. Patients were then followed in Trial 2 for 24 months after CASGEVY infusion. Patients who complete or discontinue from Trial 2 are encouraged to enroll in Trial 3 (NCT04208529), an ongoing long-term follow-up trial for additional follow-up for a total of 15 years after CASGEVY infusion.

Patients were eligible for the trial if they had a history of requiring at least 100 mL/kg/year or 10 units/year of RBC transfusions in the 2 years prior to enrollment.

Patients were excluded if they had severely elevated iron in the heart (i.e., patients with cardiac T2* less than 10 msec by magnetic resonance imaging [MRI] or left ventricular ejection fraction [LVEF] < 45% by echocardiogram) or advanced liver disease (aspartate transaminase [AST] or alanine transaminase [ALT] > 3 × the upper limit of normal [ULN], or direct bilirubin value > 2.5 × ULN, or if a liver biopsy demonstrated bridging fibrosis or cirrhosis [liver biopsy was performed if liver iron content was ≥ 15 mg/g by MRI]). Patients were also excluded if they had an available 10/10 human leukocyte antigen matched related hematopoietic stem cell donor.

At the time of the interim analysis, a total of 59 patients enrolled in the trial, of which 59 (100%) patients started mobilization. A total of 52 (88%) patients received CASGEVY infusion and formed the full analysis set (FAS). Thirty-five patients from the FAS (67%) had adequate follow-up to allow evaluation of the primary efficacy endpoint and formed the primary efficacy set (PES). The key demographics and baseline characteristics for all patients administered CASGEVY in Trial 2 are shown in Table 10, below. The baseline characteristics and demographics are consistent between the PES and the FAS.

Table 10: Demographics and baseline characteristics of patients treated with CASGEVY at the interim analysis in Trial 2
Demographics and disease characteristics | Full Analysis Set (FAS) [Interim analysis conducted based on January 2023 data cut-off date.] (N=52) | Primary Efficacy Set (PES) (N=35) [The primary efficacy set (PES), is a subset of the full analysis set (FAS). The PES was defined as all patients who had been followed for at least 16 months after CASGEVY infusion. Patients who continuously received RBC transfusions for more than 10 months after CASGEVY infusion were also included in this set.]
Age, n (%)
Adults (≥ 18 and ≤ 35 years) | 34 (65.4) | 24 (68.6)
Adolescents (≥ 12 and < 18 years) | 18 (34.6) | 11 (31.4)
All ages (≥ 12 and ≤ 35 years)
Median (min, max) | 20 (12, 35) | 20 (12, 33)
Sex, n (%)
Female | 25 (48.1) | 17 (48.6)
Male | 27 (51.9) | 18 (51.4)
Race, n (%) [Race was not collected per regional regulatory requirements in 7 (13.5%) patients in the FAS and 4 (11.4%) patients in the PES.]
Asian | 22 (42.3) | 13 (37.1)
White | 18 (34.6) | 15 (42.9)
Multiracial | 3 (5.8) | 3 (8.6)
Other | 2 (3.8) | 0
Genotype, n (%)
β^0/β^0-like [Low to no endogenous β-globin production (β^0/β^0, β^0/IVS-I-110 and IVS-I-110/IVS-I-110).] | 31 (59.6) | 20 (57.1)
Non-β^0/β^0-like | 21 (40.4) | 15 (42.9)
Baseline annualized RBC transfusion volume (mL/kg)
Median (min, max) | 201 (48, 331) | 205 (115, 331)
Baseline annualized RBC transfusion episodes
Median (min, max) | 17 (5, 35) | 17 (11, 35)
Spleen intact, n (%) | 36 (69.2) | 26 (74.3)
Baseline liver iron concentration (mg/g)
Median (min, max) | 3.5 (1.2, 14.0) | 4.0 (1.4, 14.0)
Baseline cardiac iron T2* (msec)
Median (min, max) | 34.0 (12.4, 61.1) | 34.8 (19.6, 61.1)
Baseline serum ferritin (pmol/L)
Median (min, max) | 2892 (584, 10837) | 2654 (674, 10741)

Mobilization and Apheresis

To maintain a total Hb concentration ≥ 11 g/dL, patients underwent RBC transfusions prior to mobilization and apheresis and continued receiving transfusions until the initiation of myeloablative conditioning.

To mobilize stem cells for apheresis, patients in Trial 2 were administered G-CSF and plerixafor. Patients with a spleen were administered a planned dose of 5 µg/kg G-CSF approximately every 12 hours via intravenous or subcutaneous injection for 5 to 6 days. Splenectomized patients were administered a planned dose of 5 µg/kg G-CSF once daily for 5 to 6 days. The dose was increased to every 12 hours in splenectomized patients if there was no increase in white blood cell (WBC) or peripheral blood CD34^+ counts. After 4 days of G-CSF administration, all patients received plerixafor at a planned dose of 0.24 mg/kg administered via subcutaneous injection approximately 4 to 6 hours prior to each planned apheresis.

Apheresis was carried out for up to 3 consecutive days to achieve the target collection of cells for manufacture and for the unmodified rescue CD34^+ cells.

The mean (SD) and median (min, max) number of mobilization and apheresis cycles required for manufacture CASGEVY and for the back-up collection of rescue CD34^+ cells were 1.3 (0.7) and 1 (1, 4), respectively.

Pre-treatment Conditioning

All patients received full myeloablative conditioning with busulfan prior to treatment with CASGEVY. Busulfan was administered for 4 consecutive days intravenously (IV) via a central venous catheter at a planned starting dose of 3.2 mg/kg/day once daily (qd) or 0.8 mg/kg every 6 hours (q6h). Busulfan plasma levels were measured by serial blood sampling and the dose adjusted to maintain exposure in the target range.

For the once-daily dosing, four-day target cumulative busulfan exposure was 82 mg*h/L (range: 74 to 90 mg*h/L), corresponding to AUC0-24h of 5000 µM*min (range: 4500 to 5500 µM*min). For the every 6 hours dosing, the four-day target cumulative busulfan exposure was 74 mg*h/L (range: 59 to 89 mg*h/L), corresponding to AUC0-6h of 1125 µM*min (range: 900 to 1350 µM*min).

All patients received anti-seizure prophylaxis with agents other than phenytoin prior to initiating busulfan conditioning. Phenytoin was not used for anti-seizure prophylaxis because of its induction of cytochrome P-450 and resultant increased clearance of busulfan.

Prophylaxis for hepatic veno-occlusive disease (VOD)/hepatic sinusoidal obstruction syndrome was administered, per regional and institutional guidelines.

CASGEVY Administration

Patients were administered CASGEVY with a median (min, max) dose of 7.5 (3.0, 19.7) × 10^6 CD34^+ cells/kg as an IV infusion.

All patients were administered an antihistamine and an antipyretic prior to CASGEVY infusion.

After CASGEVY Administration

G-CSF was not recommended within the first 21 days after CASGEVY infusion.

As CASGEVY is an autologous therapy, immunosuppressive agents were not required after initial myeloablative conditioning.

Efficacy Results

An interim analysis (IA) was conducted with 35 patients eligible for the primary efficacy analysis, i.e., the primary efficacy set (PES). The median (min, max) total duration of follow-up was 23.8 (16.1, 48.1) months from the time of CASGEVY infusion in the PES. There were no cases of graft failure or graft rejection.

The primary outcome was the proportion of patients achieving transfusion independence for 12 consecutive months (TI12), defined as maintaining weighted average Hb ≥ 9 g/dL without RBC transfusions for at least 12 consecutive months any time within the first 24 months after CASGEVY infusion in Trial 2, evaluated starting 60 days after the last RBC transfusion for post-transplant support or TDT disease management.

The interim analysis occurred at the time when the alpha spending was approximately 0.017 for a one-sided test, when 35 patients were evaluable for TI12 responder status. The TI12 responder rate was 32/35 (91.4%, 98.3% one-sided CI: 75.7%, 100%). All patients who achieved TI12 remained transfusion-independent, with a median (min, max) duration of transfusion-independence of 20.8 (13.3, 45.1) months and normal mean weighted average total Hb levels (mean [SD] 13.1 [1.4] g/dL). The median (min, max) time to last RBC transfusion for patients who achieved TI12 was 30 (11, 91) days following CASGEVY infusion. Three patients did not achieve TI12. These patients had reductions in annualized RBC transfusion volume requirements of 79.8%, 83.9% and 97.9%, and reductions in annualized transfusion frequency of 78.6%, 67.4% and 94.6%, respectively, compared to baseline requirements.

15 REFERENCES

1. N Engl J Med. 2021; 384:252-260 DOI: 10.1056/NEJMoa2031054

16 HOW SUPPLIED/STORAGE AND HANDLING

CASGEVY is supplied in one or more vials containing a frozen suspension of genome edited autologous CD34^+ cells in a cryopreservation medium containing 5% DMSO and dextran 40.

CASGEVY is stored in the vapor phase of liquid nitrogen and is shipped from the manufacturing facility to the treatment center storage facility in a cryoshipper. CASGEVY is supplied in vial(s) packaged in carton(s). One carton contains a single lot of CASGEVY consisting of 1 to 9 vials. A single dose of CASGEVY may consist of multiple CASGEVY lots, and therefore may consist of multiple cartons. A Lot Information Sheet listing the total dose of CASGEVY is affixed inside the shipper.

STORAGE AND HANDLING

NDC 51167-290-09

- Match the identity of the patient with the patient identifiers on each carton, vial, and Lot Information Sheet upon receipt.
- Store the vial(s) in the vapor phase of liquid nitrogen at ≤ -135 °C (≤ -211 °F) until ready for thaw and administration.
- Thaw CASGEVY prior to administration. Thaw and infuse one vial of CASGEVY at a time [see Dosage and Administration (2.2, 2.3)].
- Once thawed, CASGEVY must be administered within 20 minutes [see Dosage and Administration (2.2, 2.3)].
- Do not re-freeze CASGEVY after thawing.
- Do not irradiate CASGEVY.

17 PATIENT COUNSELING INFORMATION

Advise the patient to read the FDA-approved patient labeling (Patient Information).

Prior to treatment, advise patients of the following:

- Risks of mobilization and conditioning agents - Advise patients of the risks associated with mobilization and myeloablative conditioning agents and to read the FDA-approved patient labeling (Patient Information) for these agents.
- Potential need for additional cell collection - Ensure patients understand that if the minimum dose of CASGEVY is not met after initial product manufacturing, additional cycles of mobilization and apheresis will be needed to collect additional cells for product manufacture [see Dosage and Administration (2.2)].
- Concomitant medications - Advise patients of the need to avoid the following medications:
  - Disease modifying therapies (e.g., hydroxyurea, crizanlizumab, voxelotor) should be discontinued 8 weeks before the planned start of mobilization and conditioning [see Drug Interactions (7.2, 7.3)].
  - Iron chelation should be stopped at least 7 days prior to myeloablative conditioning. If iron chelation is required, the use of non-myelosuppressive iron chelators should be avoided for at least 3 months after CASGEVY administration and use of myelosuppressive iron chelators should be avoided for at least 6 months after CASGEVY administration. Phlebotomy can be used in lieu of iron chelation, when appropriate [see Drug Interactions (7.4)].

After treatment, advise patients of the following:

- Risk of neutrophil engraftment failure - Advise patients they will need to receive rescue treatment with their collection of unmodified CD34^+ cells if they do not achieve neutrophil engraftment after CASGEVY administration [see Dosage and Administration (2.3) and Warnings and Precautions (5.1)].
- Risk of bleeding - There is an increased risk of bleeding from initiation of myeloablative conditioning until platelet engraftment is achieved. Advise patients to monitor for signs and symptoms of new or worsening bleeding or bruising and have frequent blood draws for platelet counts, until platelet recovery has been achieved [see Warnings and Precautions (5.2)].
- Donation of blood products - Advise patients that they should not donate blood, organs, tissues, or cells at any time in the future [see Dosage and Administration (2.3)].

Manufactured for:
Vertex Pharmaceuticals Incorporated
Boston, MA 02210
US License No 2279

CASGEVY word mark and design are trademarks of Vertex Pharmaceuticals Incorporated.
VERTEX and the VERTEX triangle logo are registered trademarks of Vertex Pharmaceuticals Incorporated.
All other trademarks referenced herein are the property of their respective owners.
©2025 Vertex Pharmaceuticals Incorporated
ALL RIGHTS RESERVED

Patient Information
CASGEVY™ (cass-JEH-vee)
(exagamglogene autotemcel)
suspension for intravenous infusion

What is the most important information I should know about CASGEVY?
After treatment with CASGEVY you will have fewer blood cells for a while, until CASGEVY takes hold (engrafts) into your bone marrow. This includes low levels of platelets (cells that usually help the blood to clot) and white blood cells (cells that usually fight infections). Your doctor will monitor this and give you treatment as required. The doctor will tell you when blood cell levels return to safe levels.

- Tell your healthcare provider right away if you experience any of the following, which could be signs of low levels of platelet cells:
  - severe headache
  - abnormal bruising
  - prolonged bleeding
  - bleeding without injury such as nosebleeds, bleeding from gums, blood in your urine, stool, or vomit, or coughing up blood.

- Tell your healthcare provider right away if you experience any of the following, which could be signs of low levels of white blood cells:
  - fever
  - chills
  - infections

You may experience side effects associated with other medicines administered as part of the CASGEVY treatment regimen. Talk to your physician regarding those possible side effects. Your healthcare provider may give you other medicines to treat your side effects.

What is CASGEVY?
CASGEVY is a one-time therapy used to treat people aged 12 years and older with:

- sickle cell disease (SCD) who have frequent vaso-occlusive crises or VOCs
- beta-thalassemia (β-thal) who need regular blood transfusions.

CASGEVY is made specifically for each patient, using the patient's own edited blood stem cells, and increases the production of a special type of hemoglobin called hemoglobin F (fetal hemoglobin or HbF). Having more HbF increases overall hemoglobin levels and has been shown to improve the production and function of red blood cells. This can eliminate VOCs in people with sickle cell disease and eliminate the need for regular blood transfusions in people with β-thalassemia.

How will I receive CASGEVY?
Your healthcare provider will give you other medicines, including a conditioning medicine, as part of your treatment with CASGEVY. It's important to talk to your healthcare provider about the risks and benefits of all medicines involved in your treatment.
After receiving the conditioning medicine, it may not be possible for you to become pregnant or father a child. You should discuss options for fertility preservation with your healthcare provider before treatment.
STEP 1: Before CASGEVY treatment, a doctor will give you mobilization medicine(s). This medicine moves blood stem cells from your bone marrow into the blood stream. The blood stem cells are then collected in a machine that separates the different blood cells (this is called apheresis). This entire process may happen more than once. Each time, it can take up to one week.
During this step 'rescue cells' are also collected and stored at the hospital. These are your existing blood stem cells and are kept untreated just in case there is a problem in the treatment process. If CASGEVY cannot be given after the conditioning medicine, or if the modified blood stem cells do not take hold (engraft) in the body, these rescue cells will be given back to you. If you are given rescue cells, you will not have any treatment benefit from CASGEVY.
STEP 2: After they are collected, your blood stem cells will be sent to the manufacturing site where they are used to make CASGEVY. It may take up to 6 months from the time your cells are collected to manufacture and test CASGEVY before it is sent back to your healthcare provider.
STEP 3: Shortly before your stem cell transplant, your healthcare provider will give you a conditioning medicine for a few days in hospital. This will prepare you for treatment by clearing cells from the bone marrow, so they can be replaced with the modified cells in CASGEVY. After you are given this medicine, your blood cell levels will fall to very low levels. You will stay in the hospital for this step and remain in the hospital until after the CASGEVY infusion.
STEP 4: One or more vials of CASGEVY will be given into a vein (intravenous infusion) over a short period of time.
After the CASGEVY infusion, you will stay in hospital so that your healthcare provider can closely monitor your recovery. This can take 4-6 weeks, but times can vary. Your healthcare provider will decide when you can go home.

What should I avoid after receiving CASGEVY?

- Do not donate blood, organs, tissues, or cells at any time in the future.

What are the possible or reasonably likely side effects of CASGEVY?
The most common side effects of CASGEVY include:

- Low levels of platelet cells, which may reduce the ability of blood to clot and may cause bleeding.
- Low levels of white blood cells, which may make you more susceptible to infection.

Your healthcare provider will test your blood to check for low levels of blood cells (including platelets and white blood cells). Tell your healthcare provider right away if you get any of the following symptoms:

- fever
- chills
- infections
- severe headache
- abnormal bruising
- prolonged bleeding
- bleeding without injury such as nosebleeds, bleeding from gums, blood in your urine, stool, or vomit, or coughing up blood.

These are not all the possible side effects of CASGEVY. Call your doctor for medical advice about side effects. You may report side effects to FDA at 1-800-FDA-1088.

General information about the safe and effective use of CASGEVY
Talk to your healthcare provider about any health concerns. You can ask your healthcare provider for information about CASGEVY that is written for healthcare professionals.
For more information, go to Casgevy.com or call 1-833-837-8395.
Manufactured for: Vertex Pharmaceuticals Incorporated; 50 Northern Avenue, Boston, MA 02210
CASGEVY word mark and design are trademarks of Vertex Pharmaceuticals Incorporated.
VERTEX and the VERTEX triangle logo are registered trademarks of Vertex Pharmaceuticals Incorporated.
All other trademarks referenced herein are the property of their respective owners.
©2024 Vertex Pharmaceuticals Incorporated

This Patient Information has been approved by the U.S. Food and Drug Administration.

Revised 01/2024

PRINCIPAL DISPLAY PANEL - 20 mL Vial Carton

NDC 51167-290-09
Rx Only

exagamglogene autotemcel
casgevy™

4-13 × 10^6 CD34^+ cells/mL

suspension for IV infusion

For autologous and intravenous use only

Each vial contains autologous genome edited hematopoietic stem cells
at a concentration of 4-13 × 10^6 CD34^+ cells/mL suspended in 1.5 to 20 mL
of cryopreservation medium containing 5% DMSO and dextran 40.

The full dose is provided in one or more vial(s).

Patient ID:
V0000000

First Name:
XXXXXXXXXXXXXXXXXXXX
Last Name:
XXXXXXXXXXXXXXXXXXXX

Patient DOB:
YYYY-MMM-DD

COI ID:
000000000000000

LOT:
0000000000000
EXP:
YYYY-MMM-DD

DIN 1:
0000000000000
DIN 2:
0000000000000
DIN 3:
0000000000000

Number of vials: X

DIN 1:

DIN 2:

DIN 3:

1643-1537-1538-01